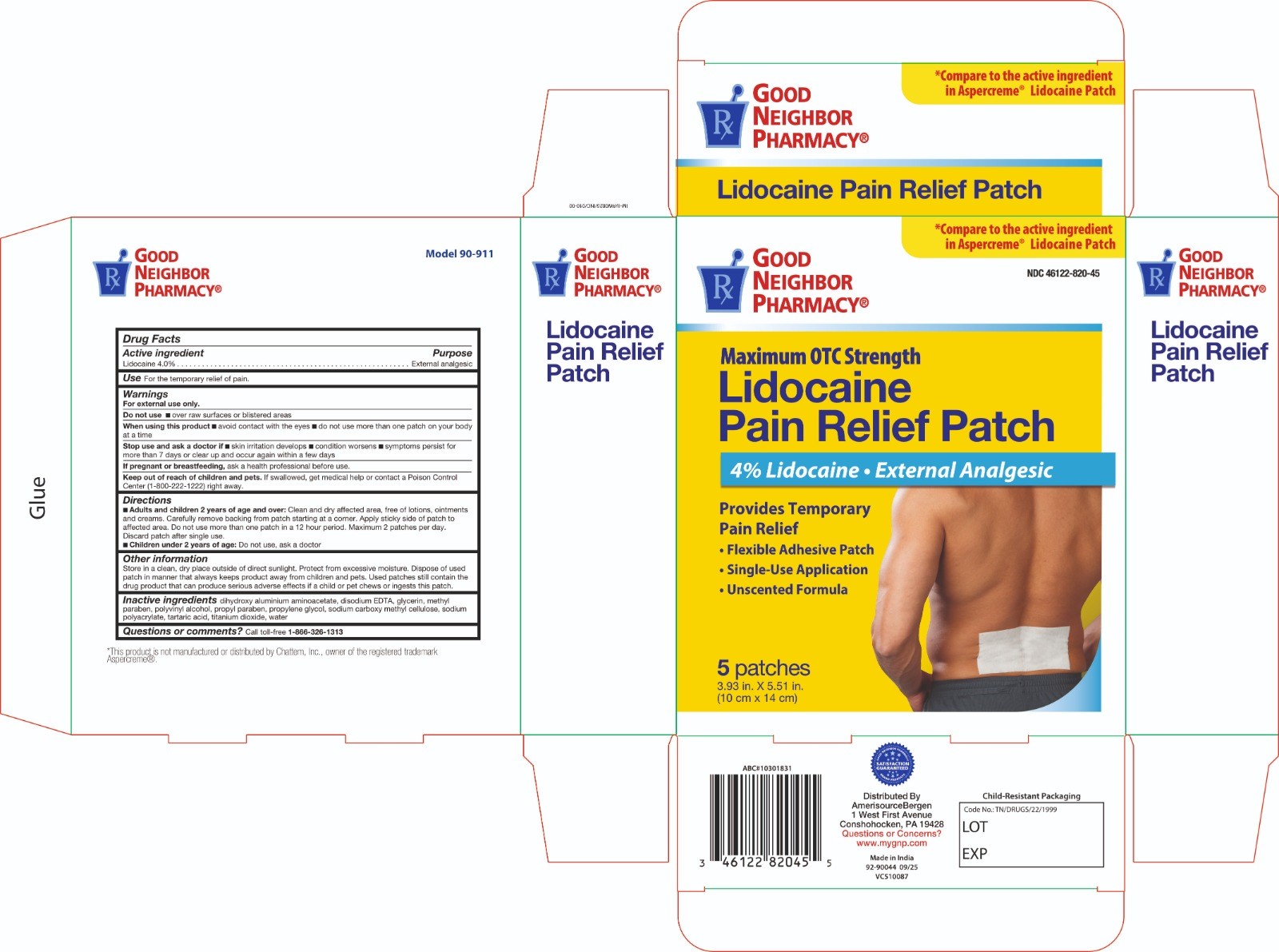 DRUG LABEL: Maximum Strength 4% Lidocaine Patch
NDC: 71811-010 | Form: PATCH
Manufacturer: InterMed Laboratories Private Limited
Category: otc | Type: HUMAN OTC DRUG LABEL
Date: 20260225

ACTIVE INGREDIENTS: LIDOCAINE 400 mg/1 1
INACTIVE INGREDIENTS: TARTARIC ACID; TITANIUM DIOXIDE; CARBOXYMETHYLCELLULOSE SODIUM; DIHYDROXYALUMINUM AMINOACETATE; GLYCERIN; EDETATE DISODIUM ANHYDROUS; METHYLPARABEN; SODIUM POLYACRYLATE (2500000 MW); PROPYLENE GLYCOL; POLYVINYL ALCOHOL, UNSPECIFIED; PROPYLPARABEN; WATER

Maximum Strength 4% Lidocaine Patch

Active Ingredient

Lidocaine 4%

Purpose

External Analgesic

Uses

For temporary relief of pain

Warnings

For external use only

Do Not Use

- more than 1 patch on your body at a time or on cut, irritated or swollen skin
- for more than one week without consulting a doctor
- over raw surfaces or blistered areas
- if pouch is damaged or opened

When Using This Product

- use only as directed. Read and follow all directions and warnings on this label.
- do not allow contact with the eyes

Stop Use and Ask a Doctor if

- condition worsens
- skin irritation develops
- symptoms persist for more than 7 days or clear up and occur again within a few days

If Pregnant or Breast Feeding

ask a health professional before use.

Keep Out of Reach of Children and Pets

If swallowed, get medical help or contact a Poison Control Center right away.

Directions

Adults and children over 2 years:

- clean and dry affected area free of lotions, ointments and creams.
- carefully remove backing from patch starting at a corner. Apply sticky side of patch to affected area.
- Do not use more than one patch in a 12 hour period. Maximum 2 patches per day. Discar patch after single use.

children 2 years or younger:ask a physician.

Inactive Ingredients

dihydroxy aluminium aminoacetate, disodium EDTA, glycerin, methyl paraben, polyvinyl alcohol, propyl paraben, propylene glycol, sodium carboxy methyl cellulose, sodium polyacrylate, tartaric acid, titanium dioxide, water